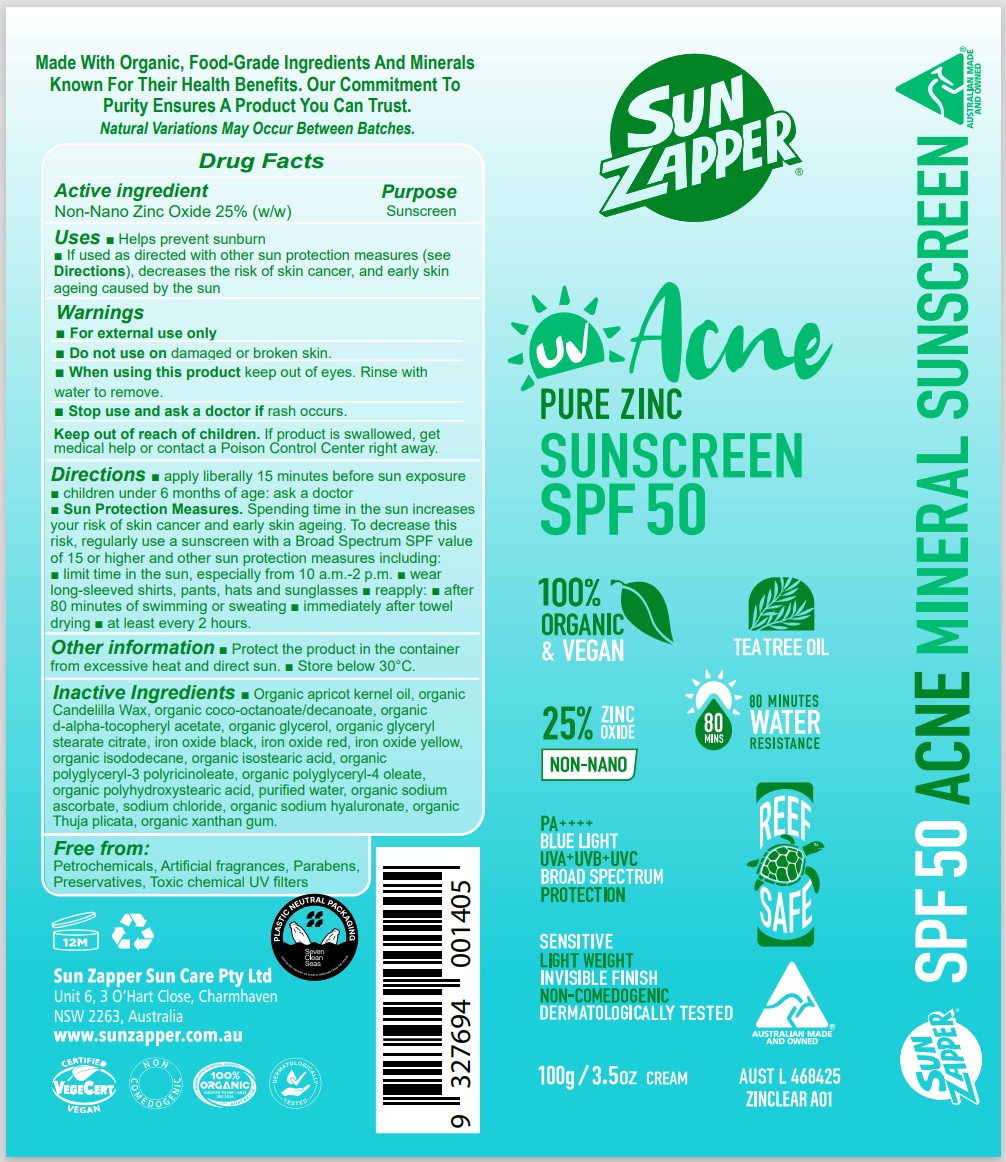 DRUG LABEL: Sun Zapper - Acne Pure Zinc Sunscreen SPF50
NDC: 83252-124 | Form: CREAM
Manufacturer: Veganic SKN Limited
Category: otc | Type: HUMAN OTC DRUG LABEL
Date: 20250916

ACTIVE INGREDIENTS: ZINC OXIDE 25 kg/100 kg
INACTIVE INGREDIENTS: MELALEUCA CAJUPUTI LEAF OIL; WATER; POLYHYDROXYSTEARIC ACID (2300 MW); SODIUM CHLORIDE; CANDELILLA WAX; ISOSTEARIC ACID; ALPHA-TOCOPHEROL ACETATE; SUNFLOWER OIL; POLYGLYCERYL-3 RICINOLEATE; POLYGLYCERYL-4 OLEATE; DINICOTINAMIDE; GLYCERYL STEARATE CITRATE

Sun Zapper - Acne Pure Zinc Sunscreen SPF50

Active ingredient: Zinc oxide 25%

Purpose: sunscreen

INDICATIONS AND USAGE

Please refer to the label

WARNINGS

Please refer to the label

KEEP OUT OF REACH OF CHILDREN

Please refer to the label

DOSAGE AND ADMINISTRATION

Please refer to the label

INACTIVE INGREDIENT

Please refer to the label